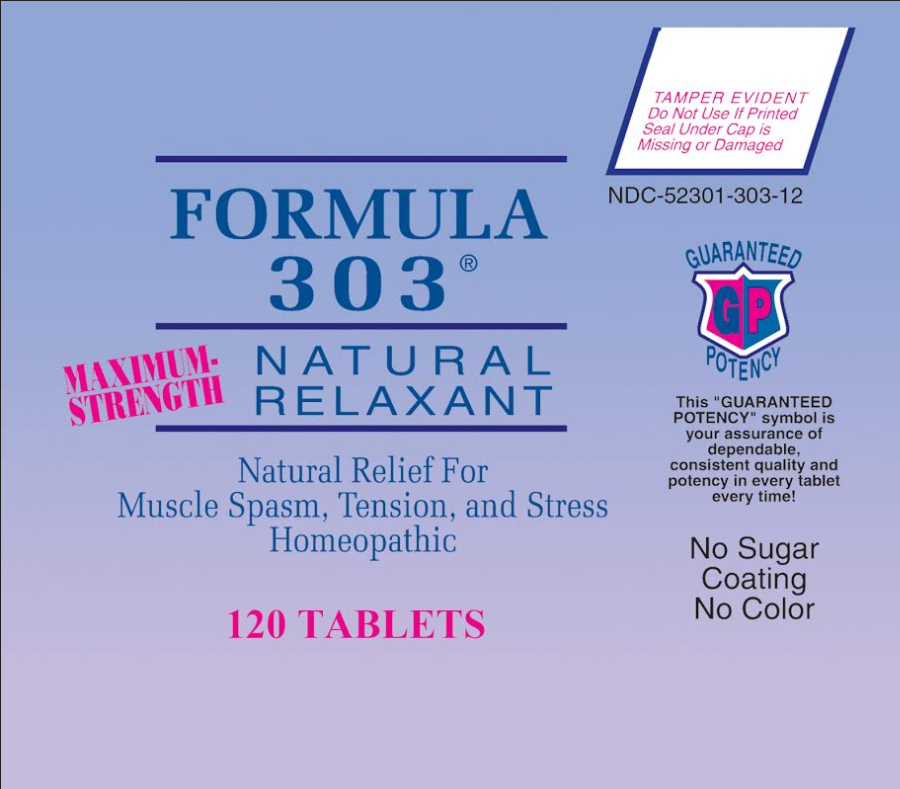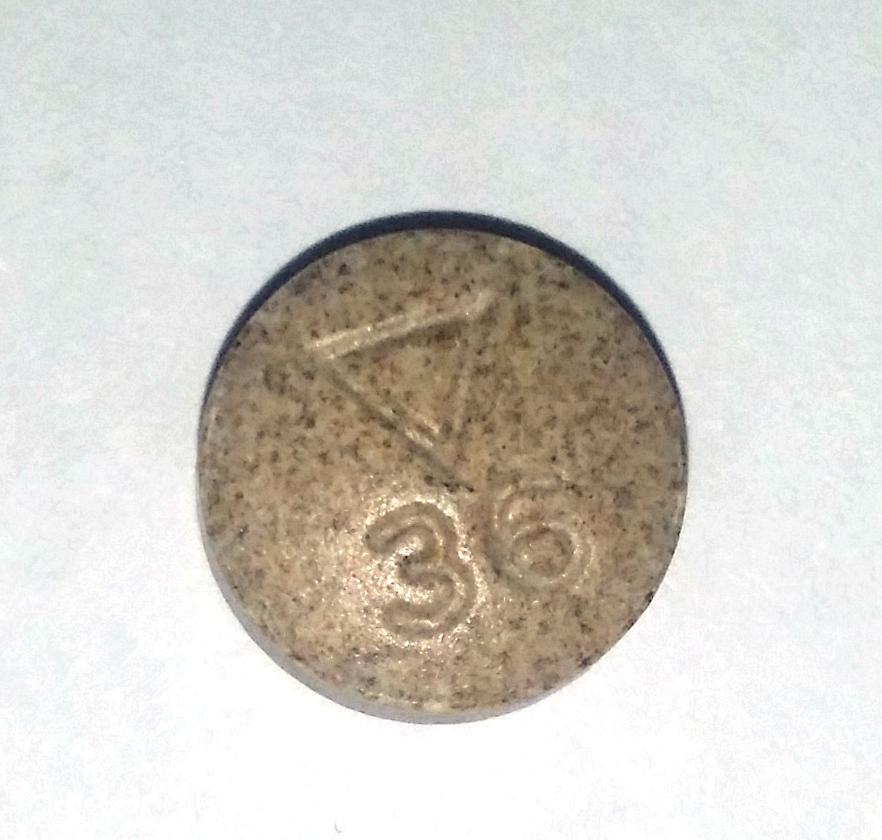 DRUG LABEL: Formula 303
NDC: 52301-303 | Form: TABLET
Manufacturer: Dee Cee Laboratories
Category: homeopathic | Type: HUMAN OTC DRUG LABEL
Date: 20250106

ACTIVE INGREDIENTS: PASSIFLORA INCARNATA FLOWER 3 [hp_X]/1 1; MAGNESIUM CARBONATE 1 [hp_X]/1 1; VALERIAN 6 [hp_X]/1 1
INACTIVE INGREDIENTS: SODIUM STARCH GLYCOLATE TYPE A POTATO; MALTODEXTRIN; LACTOSE MONOHYDRATE; STEARIC ACID; SILICON DIOXIDE

Formula 303 Maximum Strength

DOSAGE AND ADMINISTRATION

Directions: Adults and children 12 years of age and older, take as directed or as directed by your doctor. Do not exceed 12 tablets in a 24 hour period.

MUSCLE SPASM: As a muscle relaxant, two tablets every three hours until relief is obtained. Then two tablets with each meal and two at bedtime.

TENSION AND STRESS: As a relaxant, two tablets with each meal and two at bedtime.

WARNINGS

WARNING: If you are pregnant or nursing a baby, seek the advice of a healthcare professional before using this product.

PURPOSE

Natural relief for muscle spasm, tension, and stress

KEEP OUT OF REACH OF CHILDREN. In case of accidental overdose, seek professional assistance.

ACTIVE INGREDIENT

Each Tablet Contains: 6 parts Valerian Root (Quad Strength) 1X, 3 parts Passiflora (Quad Strength) 1X, 1 part Magnesium Carbonate 1X.

INDICATIONS AND USAGE

MUSCLE SPASM: As a muscle relaxant, two tablets every three hours until relief is obtained. Then two tablets with each meal and two and bedtime.

TENSION AND STRESS: As a relaxant, two tablets with each meal and two at bedtime.